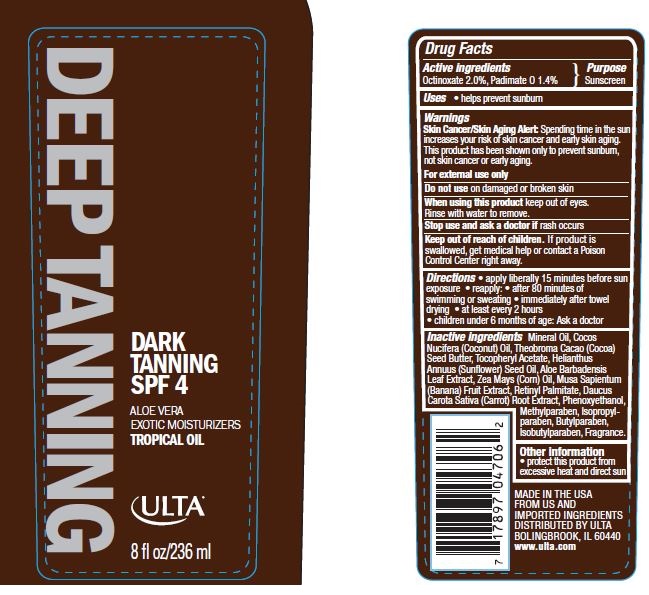 DRUG LABEL: ULTA TANNING SPF 4
NDC: 62296-7031 | Form: LOTION
Manufacturer: Ulta
Category: otc | Type: HUMAN OTC DRUG LABEL
Date: 20150803

ACTIVE INGREDIENTS: OCTINOXATE 2 g/100 g; PADIMATE O 1.4 g/100 g
INACTIVE INGREDIENTS: MINERAL OIL; COCONUT OIL; COCOA BUTTER; ALOE VERA LEAF; BANANA; VITAMIN A PALMITATE; .ALPHA.-TOCOPHEROL ACETATE; CARROT; PHENOXYETHANOL; METHYLPARABEN; ISOPROPYLPARABEN; ISOBUTYLPARABEN; BUTYLPARABEN

Drug Facts

Active ingredients

Octinoxate 2.0%, Padimate O 1.4%

Purpose

Sunscreen

Uses

- helps prevent sunburn

Warnings

Skin Cancer/Skin Aging Alert: Spending time in the sun increases your risk of skin cancer and early skin aging. This product has been shown only to prevent sunburn, not skin cancer or early aging.

For external use only

Do not use

on damaged or broken skin

When using this product

keep out of eyes. Rinse with water to remove

Stop use and ask a doctor

if rash occurs

Keep out of reach of childrem

If product is swallowed, get medical help or contact a Poison Control Center right away.

Directions

- apply liberally 15 minutes before sun exposure
- reapply after 80 minutes of swimming or sweating
- immediately after towel drying
- at least every2 hours
- children under 6 months of age: Ask a doctor

Inactive ingredients

Mineral Oil, Cocos Nucifera (Coconut) Oil, Theobroma Cacao (Cocoa) Seed Butter, Aloe Barbadensis Leaf Extract, Musa Sapientum (Banana) Fruit Extract, Retinyl Palmitate (and) Zea Mays (Corn) Oil (and) BHA (and) BHT, Tocopheryl Acetate, Daucus Carota Sativa (Carrot) Root Extract, Fragrance: Alpine Aromatics Coco Rum Banana #122-778, Phenoxyethanol (and) Methylparaben (and) Isopropylparaben (and) Isobutylparaben (and) Butylparaben.

Other information

- protect this product from excessive heat and direct sun

Principal Display panel

62296-7031-6
DEEP TANNING
DARK TANNING
SPF 4
ALOE VERA

EXOTIC MOISTURIZERS

TROPICAL OIL

ULTA

8 fl oz/ 236 ml